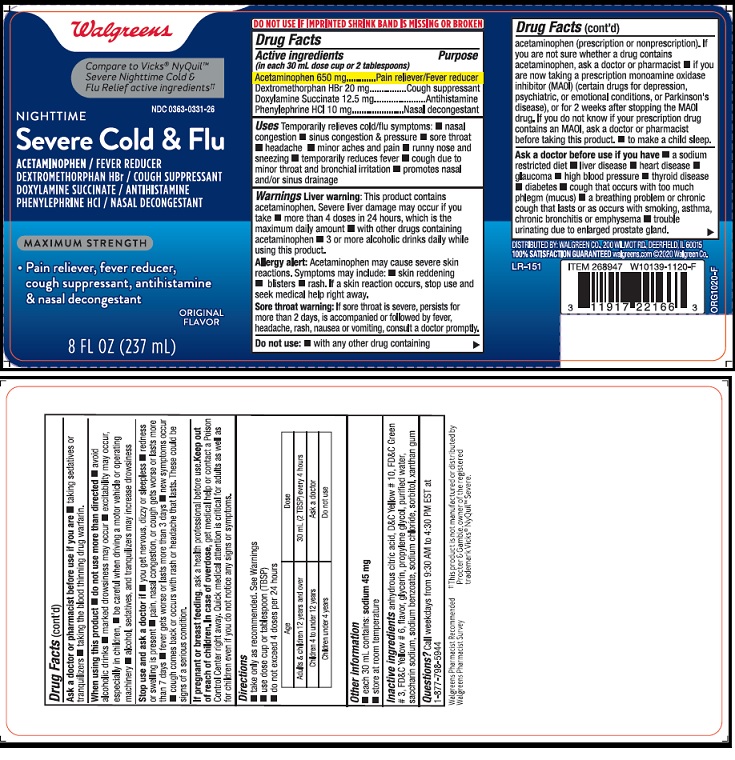 DRUG LABEL: Night Time Severe Cold and Flu
NDC: 0363-0331 | Form: LIQUID
Manufacturer: Walgreen Company
Category: otc | Type: HUMAN OTC DRUG LABEL
Date: 20231229

ACTIVE INGREDIENTS: ACETAMINOPHEN 650 mg/30 mL; DEXTROMETHORPHAN HYDROBROMIDE 20 mg/30 mL; DOXYLAMINE SUCCINATE 12.5 mg/30 mL; PHENYLEPHRINE HYDROCHLORIDE 10 mg/30 mL
INACTIVE INGREDIENTS: ANHYDROUS CITRIC ACID; D&C YELLOW NO. 10; FD&C GREEN NO. 3; FD&C YELLOW NO. 6; GLYCERIN; PROPYLENE GLYCOL; WATER; SACCHARIN SODIUM; SODIUM BENZOATE; SODIUM CHLORIDE; SORBITOL; XANTHAN GUM

Night Time Severe Cold & Flu

Drug Facts

Active ingredients
(in each 30 mL dose cup or 2 tablespoons)
Acetaminophen 650 mg
Dextromethorphan HBr 20 mg
Doxylamine Succinate 12.5 mg
Phenylephrine HCl 10 mg

Purpose
Acetaminophen ...................Pain reliever/Fever reducer
Dextromethorphan HBr........Cough suppressant
Doxylamine Succinate .........Antihistamine
Phenylephrine HCl ...............Nasal decongestant

INDICATIONS AND USAGE

Uses Temporarily relieves cold/flu symptoms: ■ nasal
congestion ■ sinus congestion & pressure ■ sore throat
■ headache ■ minor aches and pain ■ runny nose and
sneezing ■ temporarily reduces fever ■ cough due to
minor throat and bronchial irritation ■ promotes nasal
and/or sinus drainage

Warnings Liver warning: This product contains
acetaminophen. Severe liver damage may occur if you
take ■ more than 4 doses in 24 hours, which is the
maximum daily amount ■ with other drugs containing
acetaminophen ■ 3 or more alcoholic drinks daily while
using this product.

Allergy alert: Acetaminophen may cause severe skin
reactions. Symptoms may include: ■ skin reddening
■ blisters ■ rash. If a skin reaction occurs, stop use and
seek medical help right away.

Sore throat warning: If sore throat is severe, persists for
more than 2 days, is accompanied or followed by fever,
headache, rash, nausea or vomiting, consult a doctor promptly.

Do not use: ■ with any other drug containing
acetaminophen (prescription or nonprescription). If
you are not sure whether a drug contains
acetaminophen, ask a doctor or pharmacist. if you
are now taking a prescription monoamine oxidase
inhibitor (MAOI) (certain drugs for depression,
psychiatric, or emotional conditions, or Parkinson's
disease), or for 2 weeks after stopping the MAOI
drug. If you do not know if your prescription drug
contains an MAOI, ask a doctor or pharmacist
before taking this product ■ to make a child sleep.

Ask a doctor before use if you have ■ a sodium
restricted diet. liver disease ■ heart disease ■
glaucoma ■ high blood pressure ■ thyroid disease
■ diabetes. cough that occurs with too much
phlegm (mucus) ■ a breathing problem or chronic
cough that lasts or as occurs with smoking, asthma,
chronic bronchitis or emphysema. trouble
urinating due to enlarged prostate gland.

Ask a doctor of pharmacist before use if you are ■ taking sedatives or

tranquilizers ■ taking the blood thinning drug warfarin.

When using this product ■ do not use more than directed ■ avoid
alcoholic drinks ■ marked drowsiness may occur ■ excitability may occur,
especially in children, ■ be careful when driving a motor vehicle or operating
machinery ■ alcohol, sedatives, and tranquilizers may increase drowsiness.

Stop use and ask a doctor if ■ you get nervous, dizzy or sleepless ■ redness
or swelling is present ■ pain, nasal congestion, or cough gets worse or lasts more
than 7 days ■ fever gets worse or lasts more than 3 days ■ new symptoms occur
■ cough comes back or occurs with rash or headache that lasts. These could be
signs of a serious condition.

PREGNANCY OR BREAST FEEDING

If pregnant or breast-feeding, ask a health professional before use.

Keep out of reach of children. In case of overdose, get medical help or contact a Poison
Control Center right away. Quick medical attention is critical for adults as well as
for children even if you do not notice any signs or symptoms.

Directions

■ take only as recommended. See Warnings

■ use dose cup or tablespoon (TBSP)

■ do not exceed 4 doses per 24 hours

Age | Dose
Adults & children 12 years & over | 30 mL (2 TBSP) every 4 hours
Children 4 to under 12 years | Ask a doctor
Children under 4 years | Do not use

■ do not exceed 4 doses per 24 hours

Other information
■ each 30 mL contains: sodium 45 mg
■ store at room temperature

INACTIVE INGREDIENT

Inactive ingredients anhydrous citric acid, dextrose, D&C Yellow # 10, FD&C Green
# 3, FD&C Yellow # 6, flavor, glycerin, propylene glycol, purified water,
saccharin sodium, sodium benzoate, sodium chloride, sorbitol, xanthan gum

QUESTIONS

Questions? Call weekdays from 9:30 AM to 4:30 PM EST at 1-877-798-5944.

Product Label

Walgreens

Compare to Vicks® NyQuil™
Severe Nighttime Cold &
Flu Relief active ingredients††

NDC 0363-0331-26

NIGHTTIME

Severe Cold & Flu

ACETAMINOPHEN / FEVER REDUCER
DEXTROMETHORPHAN HBr / COUGH SUPPRESSANT
DOXYLAMINE SUCCINATE / ANTIHISTAMINE
PHENYLPHRINE HCl / NASAL DECONGESTANT

AMAXIMUM STRENGTH

• Pain reliever, fever reducer,
cough suppressant, antihistamine
& nasal decongestant

ORIGINAL

FLAVOR

8 FL OZ (237 mL)

DO NOT USE IF IMPRINTED SHRINK BAND IS MISSING OR TORN

DISTRIBUTED BY WALGREEN CO., 200 WILMONT RD., DEERFIELD, IL 60015

100 % SATISFACTION GUARANTEED walgreens.com@2020WalgreenVo.

LR-151

ORG1020-F

res